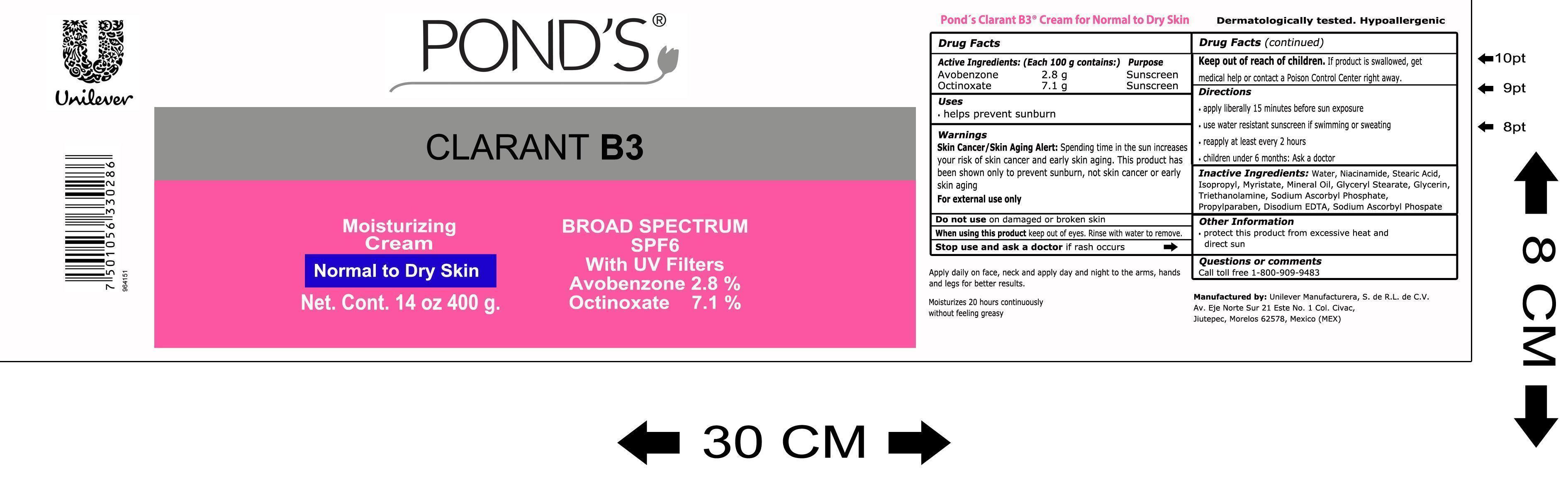 DRUG LABEL: Clarant B3
NDC: 51769-614 | Form: CREAM
Manufacturer: ALL NATURAL DYNAMICS
Category: otc | Type: HUMAN OTC DRUG LABEL
Date: 20140704

ACTIVE INGREDIENTS: Avobenzone 2800 mg/100 g; Octinoxate 7100 mg/100 g
INACTIVE INGREDIENTS: Water; Niacinamide; Stearic Acid; Isopropyl Myristate; Mineral Oil; Glyceryl Monostearate; Glycerin; Trolamine; Propylparaben; Edetate Disodium; Sodium Ascorbyl Phosphate

Clarant B3 Normal to Dry Skin

Active Ingredients

Avobenzone
Octinoxate

Active Ingredients: (Each 100 g contains:) Purpose

Avobenzone 2.8 g Sunscreen
Octinoxate 7.1 g Sunscreen

Warnings

Skin Cancer/Skin Aging Alert: Spending time in the sun increases your risk of skin cancer and early skin aging. This product has been shown only to prevent sunburn, not skin cancer or early skin aging

For external use only

Uses

• helps prevent sunburn

Do not use

on damaged or broken skin

When using this product

keep out of eyes. Rinse with water to remove

Stop use and ask a doctor

if rash occurs

Keep out of reach of children.

If product is swallowed, get medical help or contact a Poison Control Center right away.

Inactive ingredients:

Water, Niacinamide, Stearic Acid, Isopropyl Myristate, Mineral Oil, Glyceryl Stearate, Glycerin, Triethanolamine, Sodium Ascorbyl Phosphate, Propylparaben,Disodium EDTA, Sodium Ascorbyl Phosphate